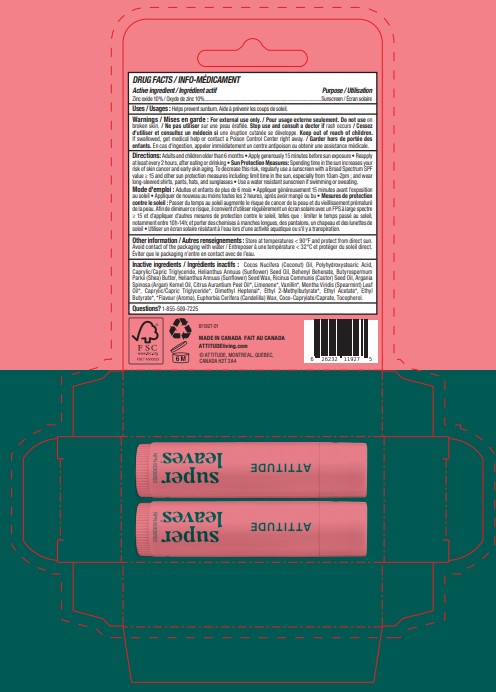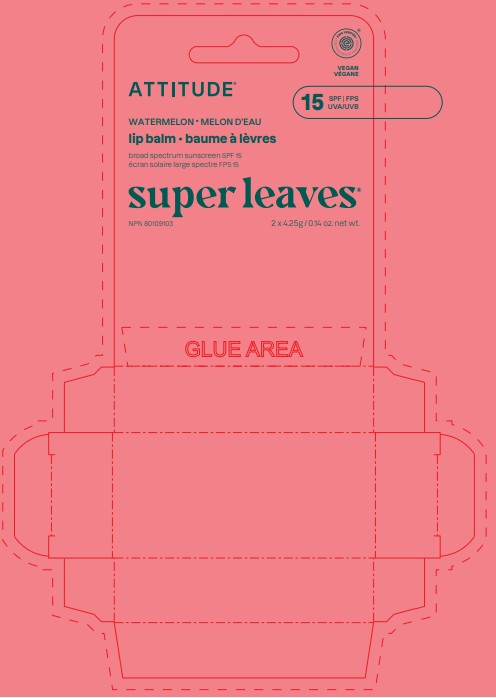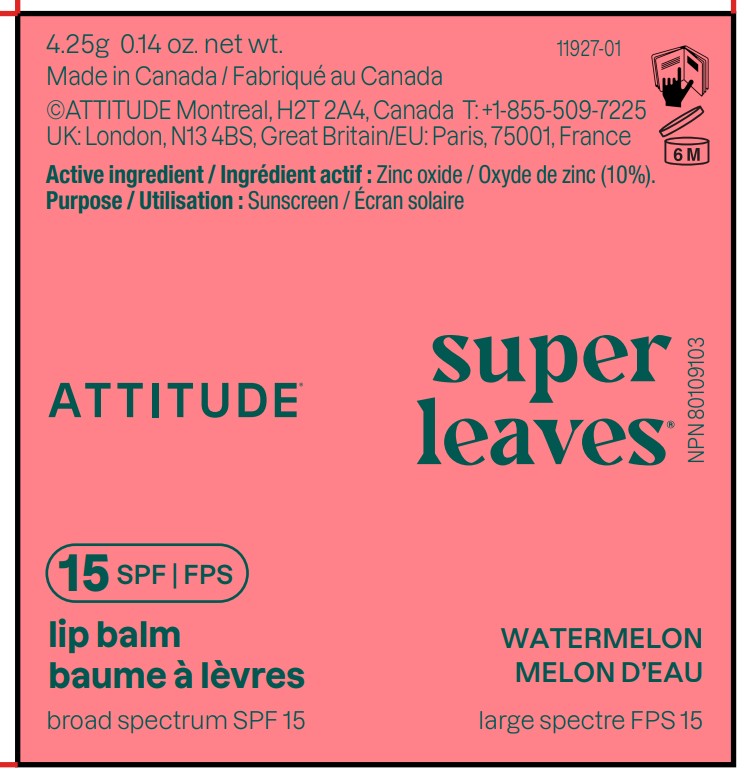 DRUG LABEL: ATTITUDE Super leaves Lip Balm SPF 15 Watermelon
NDC: 61649-927 | Form: STICK
Manufacturer: 9055-7588 Québec Inc.DBA ATTITUDE
Category: otc | Type: HUMAN OTC DRUG LABEL
Date: 20251203

ACTIVE INGREDIENTS: ZINC OXIDE 10 g/100 g
INACTIVE INGREDIENTS: CITRUS AURANTIUM PEEL OIL; ETHYL 2-METHYLBUTYRATE; RICINUS COMMUNIS (CASTOR) SEED OIL; EUPHORBIA CERIFERA (CANDELILLA) WAX; ARGANIA SPINOSA KERNEL OIL; BEHENYL BEHENATE; CAPRYLIC/CAPRIC TRIGLYCERIDE; COCO-CAPRYLATE/CAPRATE; HELIANTHUS ANNUUS (SUNFLOWER) SEED WAX; HELIANTHUS ANNUUS (SUNFLOWER) SEED OIL; BUTYROSPERMUM PARKII (SHEA) BUTTER; COCOS NUCIFERA (COCONUT) OIL; TOCOPHEROL; POLYHYDROXYSTEARIC ACID (2300 MW); ETHYL ACETATE; LIMONENE, (+/-)-; ETHYL BUTYRATE; MENTHA VIRIDIS (SPEARMINT) LEAF OIL; VANILLIN; DIMETHYL HEPTENAL

ATTITUDE Super leaves Lip Balm SPF 15 Watermelon

DRUG FACTS

ACTIVE INGREDIENT

Zinc oxide (10 %)

PURPOSE

Sunscreen

INDICATIONS AND USAGE

Helps prevent sunburn

WARNINGS

For external use only.

Do not use on broken skin.

Keep out of reach of children. If swallowed, get medical help or contact a Poison Control Center right away.

Stop use and consult a doctor if rash occurs.

DOSAGE AND ADMINISTRATION

Adults and children older than 6 months • Apply generously 15 minutes before sun exposure • Reapply at least every 2 hours, after eating or drinking • Sun Protection Measures: Spending time in the sun increases your risk of skin cancer and early skin aging. To decrease this risk, regularly use a sunscreen with a Broad Spectrum SPF value ≥ 15 and other sun protection measures including: limit time in the sun, especially from 10am-2pm ; and wear long-sleeved shirts, pants, hats, and sunglasses • Use a water resistant sunscreen if swimming or sweating.

INACTIVE INGREDIENT

Cocos Nucifera (Coconut) Oil, Polyhydroxystearic Acid, Caprylic/Capric Triglyceride, Helianthus Annuus (Sunflower) Seed Oil, Behenyl Behenate, Butyrospermum Parkii (Shea) Butter, Helianthus Annuus (Sunflower) Seed Wax, Ricinus Communis (Castor) Seed Oil, Argania Spinosa (Argan) Kernel Oil, Citrus Aurantium Peel Oil*, Limonene*, Vanillin*, Mentha Viridis (Spearmint) Leaf Oil*, Caprylic/Capric Triglyceride*, Dimethyl Heptenal*, Ethyl 2-Methylbutyrate*, Ethyl Acetate*, Ethyl Butyrate*, *Flavour (Aroma), Euphorbia Cerifera (Candelilla) Wax, Coco-Caprylate/Caprate, Tocopherol.

STORAGE AND HANDLING

Store at temperatures < 90°F and protect from direct sun. Avoid contact of the packaging with water

Questions ? 1-855-509-7225

PACKAGE LABEL

ATTITUDE

EWG Verified

VEGAN

SPF 15

UVA ¦ UVB

watermelon

lip balm

Broad spectrum sunscreen SPF 15

Super leaves

2 x 4.25 g / 0.14 oz. net wt.

NPN 80109103

Made in Canada